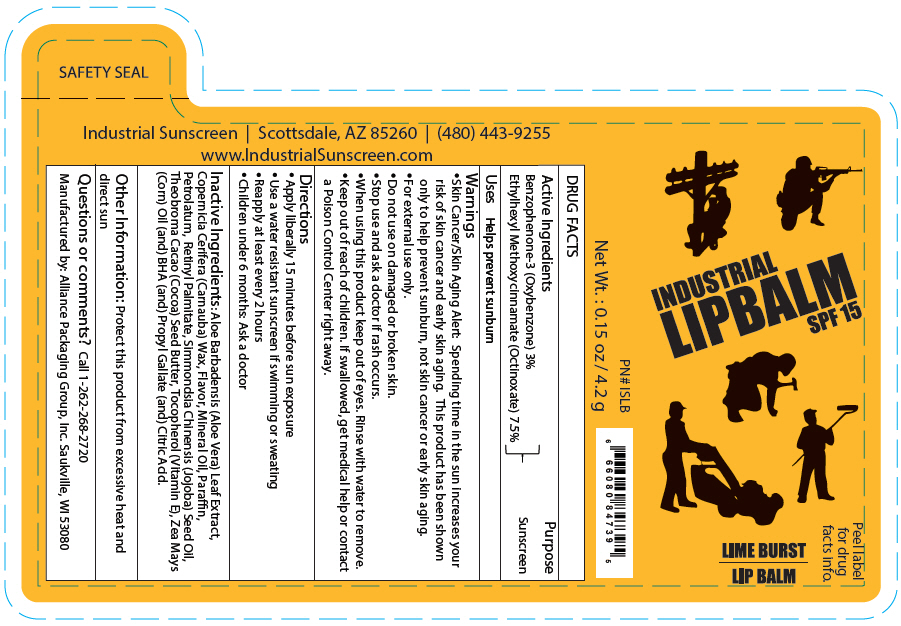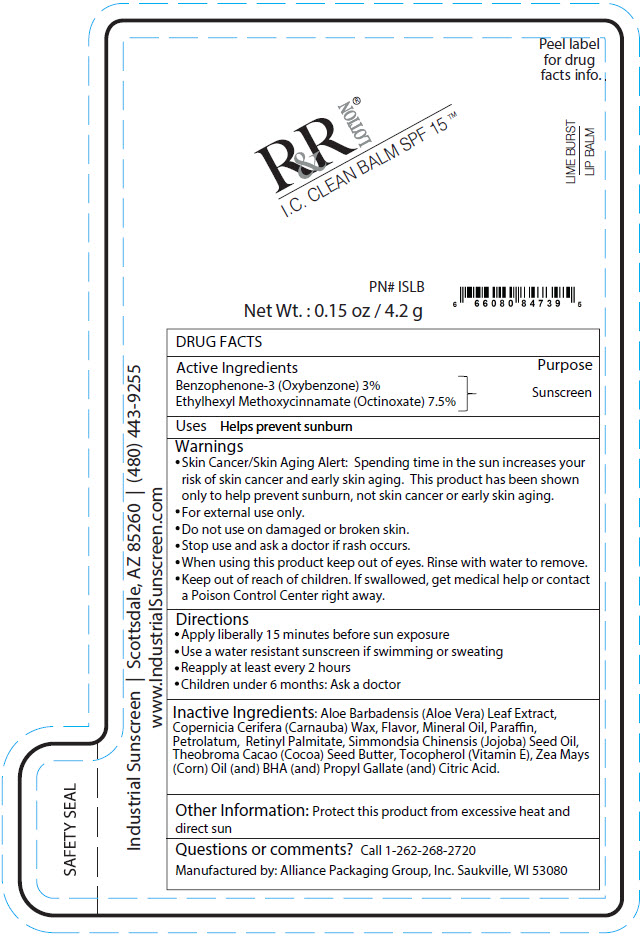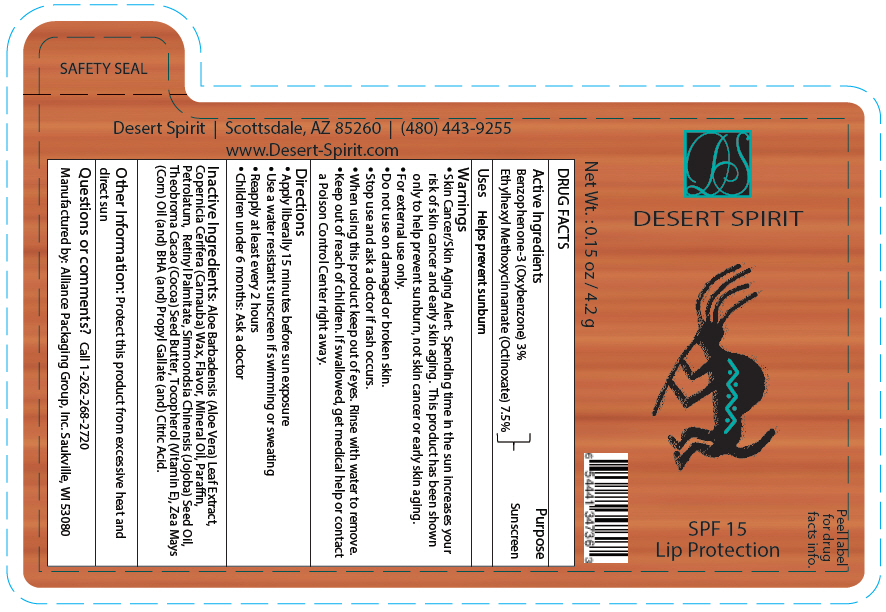 DRUG LABEL: Industrial  Lip Balm SPF 15
NDC: 59555-111 | Form: LIPSTICK
Manufacturer: R & R Lotion, Inc
Category: otc | Type: HUMAN OTC DRUG LABEL
Date: 20201020

ACTIVE INGREDIENTS: Octinoxate 75 mg/1 g; Oxybenzone 30 mg/1 g
INACTIVE INGREDIENTS: WATER; Carnauba Wax; Mineral Oil; Paraffin; Petrolatum; Vitamin A Palmitate; Jojoba Oil; Cocoa Butter; Corn Oil; Propyl Gallate; Citric Acid Monohydrate; BUTYLATED HYDROXYANISOLE

Lip Balm SPF 15

DRUG FACTS

Active Ingredients

Benzophenone-3 (Oxybenzone) 3%
Ethylhexyl Methoxycinnamate (Octinoxate) 7.5%

Purpose

Sunscreen

Uses

Helps prevent sunburn

Warnings

- Skin Cancer/Skin Aging Alert: Spending time in the sun increases your risk of skin cancer and early skin aging. This product has been shown only to help prevent sunburn, not skin cancer or early skin aging.
- For external use only.

- Do not use on damaged or broken skin.

- Stop use and ask a doctor if rash occurs.

- When using this product keep out of eyes. Rinse with water to remove.

- Keep out of reach of children. If swallowed, get medical help or contact a Poison Control Center right away.

Directions

- Apply liberally 15 minutes before sun exposure
- Use a water resistant sunscreen if swimming or sweating
- Reapply at least every 2 hours
- Children under 6 months: Ask a doctor

Inactive Ingredients

Aloe Barbadensis (Aloe Vera) Leaf Extract, Copernicia Cerifera (Carnauba) Wax, Flavor, Mineral Oil, Paraffin, Petrolatum, Retinyl Palmitate, Simmondsia Chinensis (Jojoba) Seed Oil, Theobroma Cacao (Cocoa) Seed Butter, Tocopherol (Vitamin E), Zea Mays (Corn) Oil (and) BHA (and) Propyl Gallate (and) Citric Acid.

Other Information

Protect this product from excessive heat and direct sun

Questions or comments?

Call 1-262-268-2720

Manufactured by: Alliance Packaging Group, Inc. Saukville, WI 53080

PRINCIPAL DISPLAY PANEL - 4.2 g Applicator Label - Industrial

INDUSTRIAL
LIPBALM
SPF 15

LIME BURST
LIP BALM

PN# ISLB

Net Wt. : 0.15 oz / 4.2 g

Peel label
for drug
facts info.

PRINCIPAL DISPLAY PANEL - 4.2 g Applicator Label - Clean Balm

Peel label
for drug
facts info.

R&R
LOTION®
I.C. CLEAN BALM SPF 15 ™

LIME BURST
LIP BALM

PN# ISLB

Net Wt. : 0.15 oz / 4.2 g

PRINCIPAL DISPLAY PANEL - 4.2 g Applicator Label - Desert Spirit

DESERT SPIRIT

SPF 15
Lip Protection

Net Wt. : 0.15 oz / 4.2 g

Peel label
for drug
facts info.